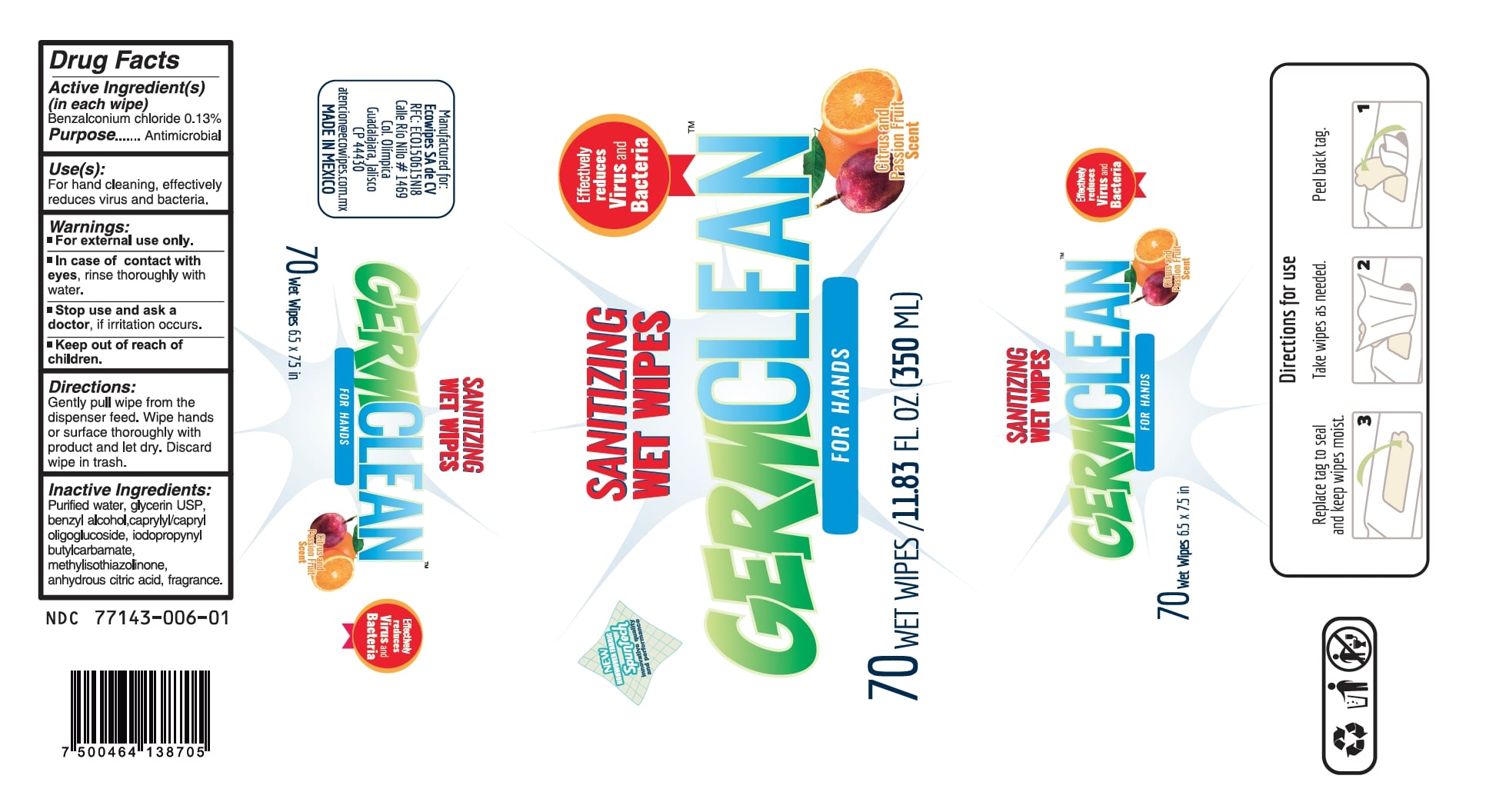 DRUG LABEL: GERM CLEAN
NDC: 77143-006 | Form: CLOTH
Manufacturer: NATURATLALI S DE RL DE CV
Category: otc | Type: HUMAN OTC DRUG LABEL
Date: 20201127

ACTIVE INGREDIENTS: BENZALKONIUM CHLORIDE 0.13 g/100 mL
INACTIVE INGREDIENTS: GLYCERIN 0.7 mL/100 mL; IODOPROPYNYL BUTYLCARBAMATE 0.0625 mL/100 mL; WATER; BENZYL ALCOHOL 1 mL/100 mL; CITRIC ACID MONOHYDRATE 0.003 mL/100 mL; CAPRYLYL/CAPRYL OLIGOGLUCOSIDE 0.125 mL/100 mL; GLYCERYL OLEATE 0.125 mL/100 mL; METHYLISOTHIAZOLINONE 0.0625 mL/100 mL; FRAGARIA VESCA FRUIT JUICE 0.04 mL/100 mL; FRAGRANCE LEMON ORC2001060 0.08 mL/100 mL

77143-006
Toallitas sanitizantes

Active Ingredient(s)

Benzalkonium chloride 0.13% w/w. Purpose: Antiseptic

Purpose

Antiseptic, Hand Sanitizer

Use

Hand Sanitizer to help reduce bacteria that potentially can cause disease. For use when soap and water are not available.

Warnings

For external use only.

WHEN USING

In case of contact with eyes, rinse eyes thoroughly with water.
Stop use and ask a doctor if irritation or rash occurs.
Keep out of reach of children.

Stop use and ask a doctor if irritation or rash occurs. These may be signs of a serious condition.

Keep out of reach of children. If swallowed, get medical help or contact a Poison Control Center right away.

Directions

- Gently pull wipe from the dispenser feed.
- Wipe hands thoroughly with product and let dry.
- Discard wipe in trash.

Other information

- Store between 15-30C (59-86F)
- Avoid freezing and excessive heat above 40C (104F)

Inactive ingredients

purified water, glycerin USP, benzyl alcohol, caprylyl/capryl oligoglucoside, iodopropynyl butylcarbamate, methylisothiazolinone, anhydrous citric acid, fragrance.

Package Label - Principal Display Panel

350 mL NDC: 77143-006-01